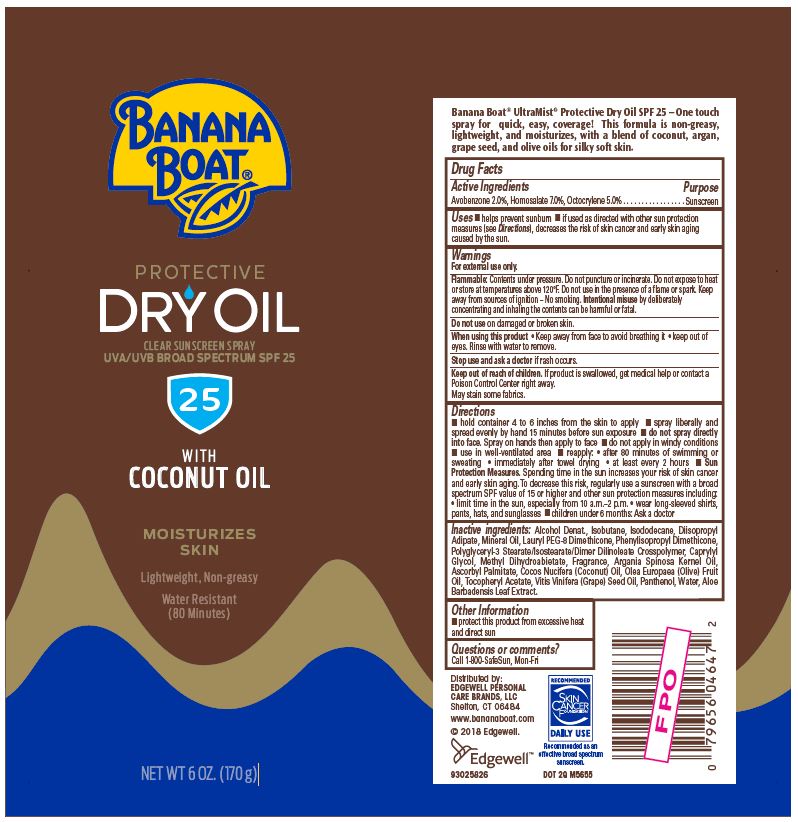 DRUG LABEL: BANANA BOAT
NDC: 63354-353 | Form: SPRAY
Manufacturer: Edgewell Personal Care Brands, LLC
Category: otc | Type: HUMAN OTC DRUG LABEL
Date: 20231116

ACTIVE INGREDIENTS: HOMOSALATE 7 g/100 g; OCTOCRYLENE 5 g/100 g; AVOBENZONE 2 g/100 g
INACTIVE INGREDIENTS: ARGAN OIL; PANTHENOL; WATER; DIISOPROPYL ADIPATE; ASCORBYL PALMITATE; METHYL DIHYDROABIETATE; ALOE VERA LEAF; MINERAL OIL; ALCOHOL; ISOBUTANE; ISODODECANE; CAPRYLYL GLYCOL

Active Ingredients

Avobenzone 2.0%, Homosalate 7.0%, Octocrylene 5.0%

Purpose

Sunscreen

Uses

helps prevent sunburn. if used as directed with other sun protection measures (see Directions), decreases the risk of skin cancer and early skin aging caused by the sun.

Warnings

For external use only.

Flammable: Do not puncture or incinerate. Contents under pressure. Do not expose to heat or store at temperatures above 120F. Do not use in the presence of a flame or spark. Keep away from sources of ignition-No smoking. Intentional misuse by deliberately concentrating and inhaling the contents can be harmful or fatal.

May stain some fabrics.

Do not use

on damaged or broken skin.

When using this product

Keep away from face to avoid breathing it. keep out of eyes. Rinse with water to remove.

Stop use and ask a doctor

if rash occurs.

Keep out of reach of children.

If product is swallowed, get medical help or contact a Poison Control Center right away.

Directions

• hold container 4 to 6 inches from the skin to apply. • spray liberally and spread evenly by hand 15 minutes before sun exposure. • do not spray directly into face. Spray on hands then apply to face. • do not apply in windy conditions. • use in well-ventilated area. • reapply: • after 80 minutes of swimming or sweating, • immediately after towel drying, • at least every 2 hours. • Sun Protection Measures. Spending time in the sun increases your risk of skin cancer and early skin aging. To decrease this risk, regularly use a sunscreen with a broad spectrum SPF of 15 or higher and other sun protection measures including: • limit time in the sun, especially from 10 a.m.-2 p.m., • wear long-sleeved shirts, pants, hats, and sunglasses. children under 6 months: Ask a doctor.

Inactive ingredients

Alcohol Denat., Isobutane, Isododecane, Diisopropyl Adipate, Mineral Oil, Lauryl PEG-8 Dimethicone, Phenylisopropyl Dimethicone, Polyglyceryl-3 Stearate/Isostearate/Dimer Dilinoleate Crosspolymer, Caprylyl Glycol, Methyl Dihydroabietate, Fragrance, Argania Spinosa Kernel Oil, Ascorbyl Palmitate, Cocos Nucifera (Coconut) Oil, Olea Europaea (Olive) Fruit Oil, Tocopheryl Acetate, Vitis Vinifera (Grape) Seed Oil, Panthenol, Water, Aloe Barbadensis Leaf Extract.

Other Information

protect this product from excessive heat and direct sun

Questions or comments?

Call 1 800 SafeSun, Mon-Fri

PACKAGE LABEL

BANANA
BOAT®
PROTECTIVE
DRY OIL
CLEAR SUNSCREEN SPRAY
UVA/UVB BROAD SPECTRUM SPF 25
25
WITH
COCONUT OIL
MOISTURIZES
SKIN
Lightweight, Non-greasy
Water Resistant
(80 Minutes)
NET WT 6 OZ. (170 g)